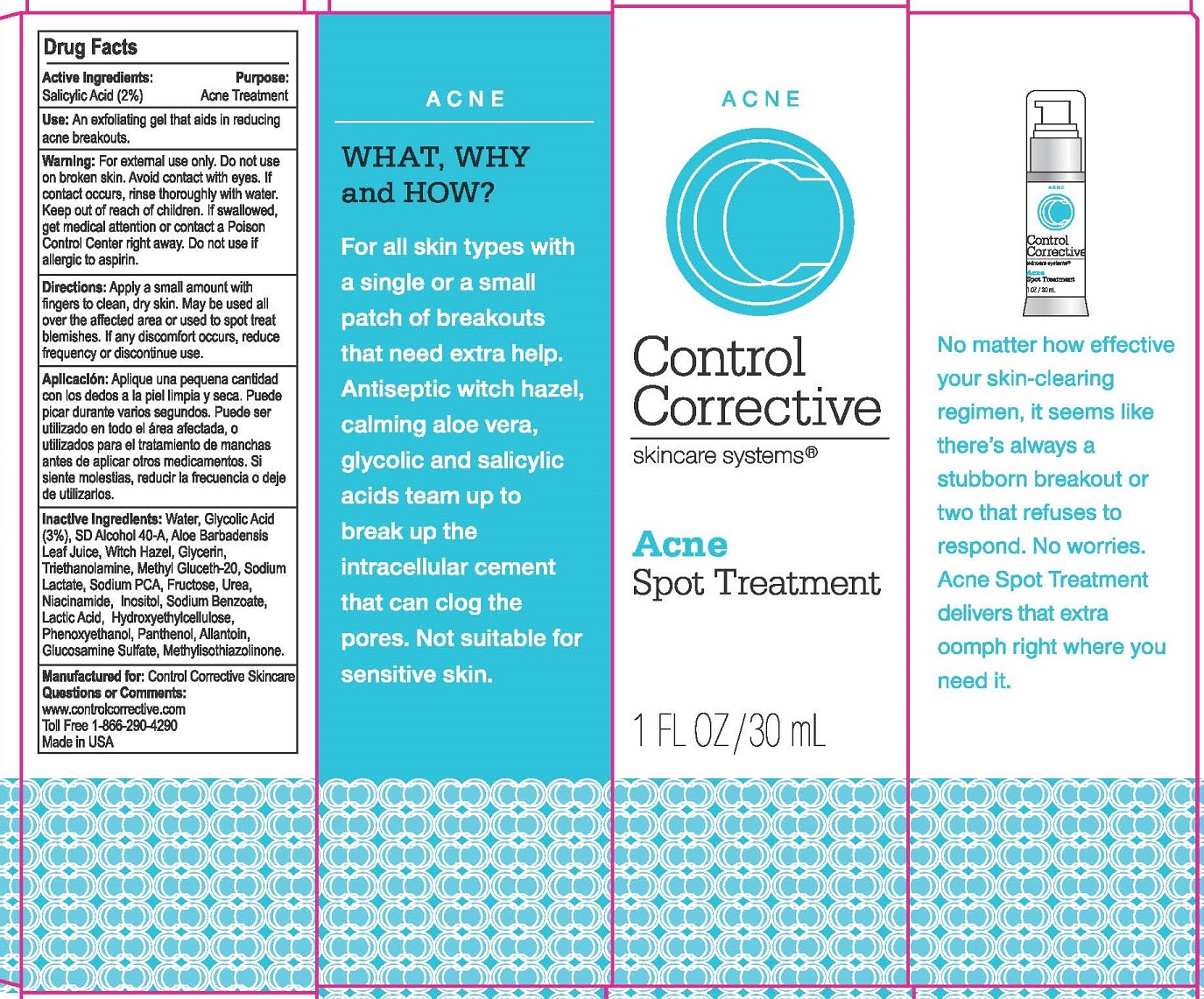 DRUG LABEL: ACNE SPOT TREATMENT
NDC: 70764-105 | Form: GEL
Manufacturer: CONTROL CORRECTIVE SKINCARE INC
Category: otc | Type: HUMAN OTC DRUG LABEL
Date: 20251231

ACTIVE INGREDIENTS: SALICYLIC ACID 2 g/100 mL
INACTIVE INGREDIENTS: WATER; GLYCOLIC ACID; ALCOHOL; ALOE VERA LEAF; WITCH HAZEL; GLYCERIN; TROLAMINE; METHYL GLUCETH-20; SODIUM LACTATE; SODIUM PYRROLIDONE CARBOXYLATE; FRUCTOSE; UREA; NIACINAMIDE; INOSITOL; SODIUM BENZOATE; LACTIC ACID; HYDROXYETHYL CELLULOSE (100 MPA.S AT 2%); PHENOXYETHANOL; PANTHENOL; ALLANTOIN; GLUCOSAMINE SULFATE; METHYLISOTHIAZOLINONE

CONTROL CORRECTIVE (70764-105)

ACTIVE INGREDIENTS

SALICYLIC ACID (2.0%)

PURPOSE

ACNE TREATMENT

USE

AN EXFOLIATING GEL THAT AIDS IN REDUCING ACNE BREAKOUTS.

WARNINGS

FOR EXTERNAL USE ONLY. DO NOT USE ON BROKEN SKIN. AVOID CONTACT WITH EYES. IF CONTACT OCCURS, RINSE THOROUGHLY WITH WATER.

DIRECTIONS

APPLY A SMALL AMOUNT WITH FINGERS TO CLEAN, DRY SKIN. MAY BE USED ALL OVER THE AFFECTED AREA OR USED TO SPOT TREAT BLEMISHES. IF ANY DISCOMFORT OCCURS, REDUCE FREQUENCY OR DISCONTINUE USE.

INACTIVE INGREDIENTS

WATER, GLYCOLIC ACID (3%), SD ALCOHOL 40-A, ALOE BARBADENSIS LEAF JUICE, WITCH HAZEL, GLYCERIN, TRIETHANOLAMINE, METHYL GLUCETH-20, SODIUM LACTATE, FRUCTOSE, UREA, NIACINAMIDE, INOSITOL, SODIUM BENZOATE, LACTIC ACID, HYDROXYETHYLCELLULOSE, PHENOXYETHANOL, PANTHENOL, ALLANTOIN, GLUCOSAMINE SULFATE, METHYLISOTHIAZOLINONE.

KEEP OUT OF REACH OF CHILDREN. IF SWALLOWED, GET MEDICAL HELP OR CONTACT A POISON CONTROL CENTER RIGHT AWAY.

DO NOT USE IF ALLERGIC TO ASPERIN.

QUESTIONS OR COMMENTS:

WWW.CONTROLCORRECTIVE.COM

TOLL FREE 1-866-290-4290

MADE IN USA